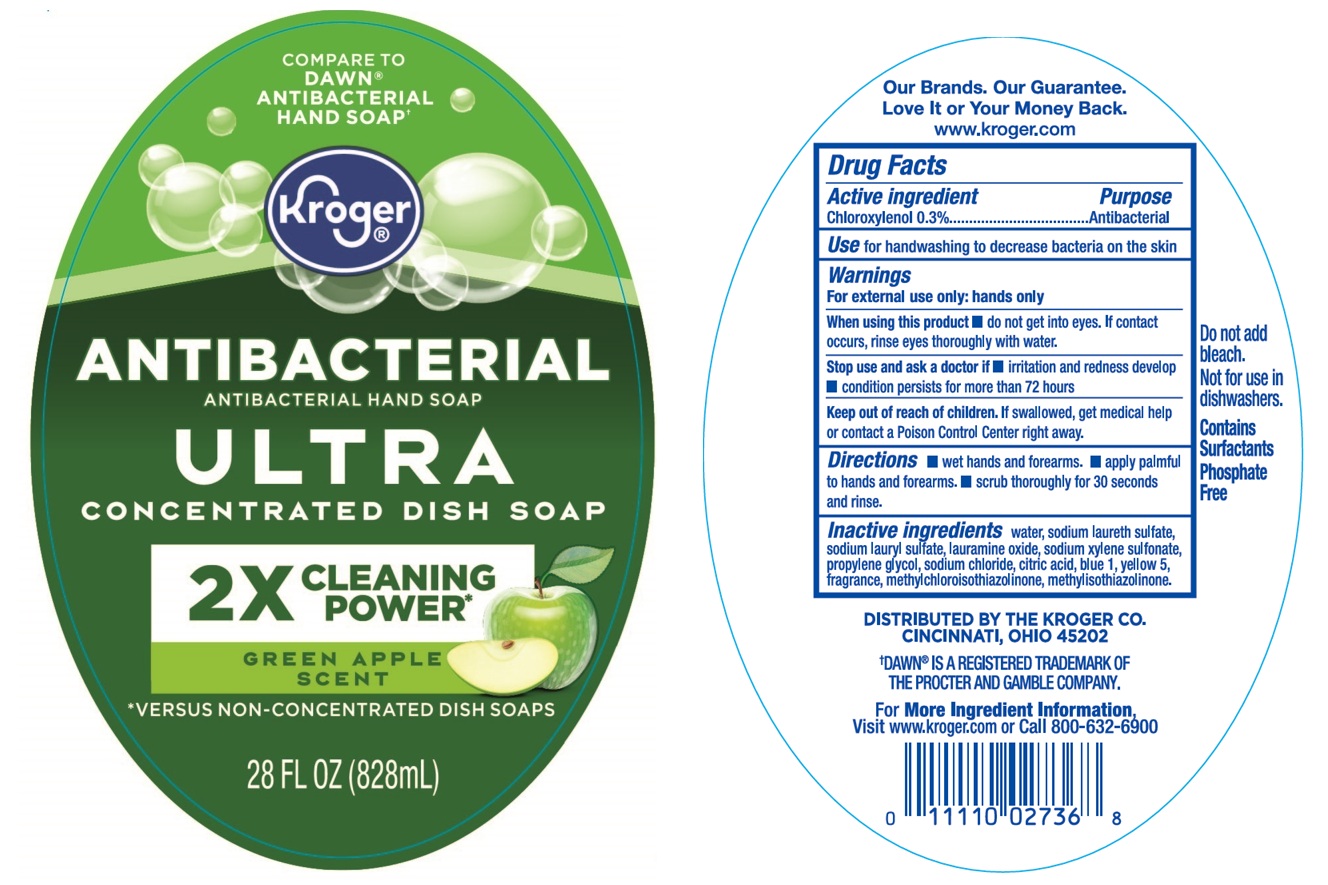 DRUG LABEL: Kroger Antibacterial Green Apple Hand
NDC: 73487-001 | Form: SOAP
Manufacturer: Korex Chicago LLC
Category: otc | Type: HUMAN OTC DRUG LABEL
Date: 20251215

ACTIVE INGREDIENTS: CHLOROXYLENOL 0.3 g/100 mL
INACTIVE INGREDIENTS: WATER; SODIUM LAURETH-3 SULFATE; SODIUM LAURYL SULFATE; LAURAMINE OXIDE; SODIUM XYLENESULFONATE; PROPYLENE GLYCOL; SODIUM CHLORIDE; CITRIC ACID MONOHYDRATE; FD&C BLUE NO. 1; FD&C YELLOW NO. 5; METHYLCHLOROISOTHIAZOLINONE; METHYLISOTHIAZOLINONE

Kroger® ANTIBACTERIAL HAND SOAP GREEN APPLE SCENT

Active ingredient

Chloroxylenol 0.3%

Purpose

Antibacterial

Use

for handwashing to decrease bacteria on the skin

Warnings

For external use only: hands only

When using this product • do not get into eyes. If contact occurs, rinse eyes thoroughly with water.

Stop use and ask a doctor if • irritation and redness develop • condition persists for more than 72 hours

Keep out of reach of children. If swallowed, get medical help or contact a Poison Control Center right away.

Directions

• wet hands and forearms. • apply palmful to hands and forearms. • scrub thoroughly for 30 seconds and rinse.

Inactive ingredients

water, sodium laureth sulfate, sodium lauryl sulfate, lauramine oxide, sodium xylene sulfonate, propylene glycol, sodium chloride, citric acid, blue 1, yellow 5, fragrance, methylchloroisothiazolinone, methylisothiazolinone.

COMPARE TO DAWN® ANTIBACTERIAL HAND SOAP†

ULTRA CONCENTRATED DISH SOAP

2X CLEANING POWER

GREEN APPLE SCENT

*VERSUS NON-CONCENTRATED DISH SOAPS

Our Brands. Our Guarantee.
Love It or Your Money Back.

Do not add bleach. Not for use in dishwashers.

Contains surfactants
Phosphate Free

DISTRIBUTED BY THE KROGER CO.
CINCINNATI, OHIO 45202

†DAWN® IS A REGISTERED TRADEMARK OF THE PROCTER AND GAMBLE COMPANY.

For More Ingredient Information,
Visit www.kroger.com or call 800-632-6900